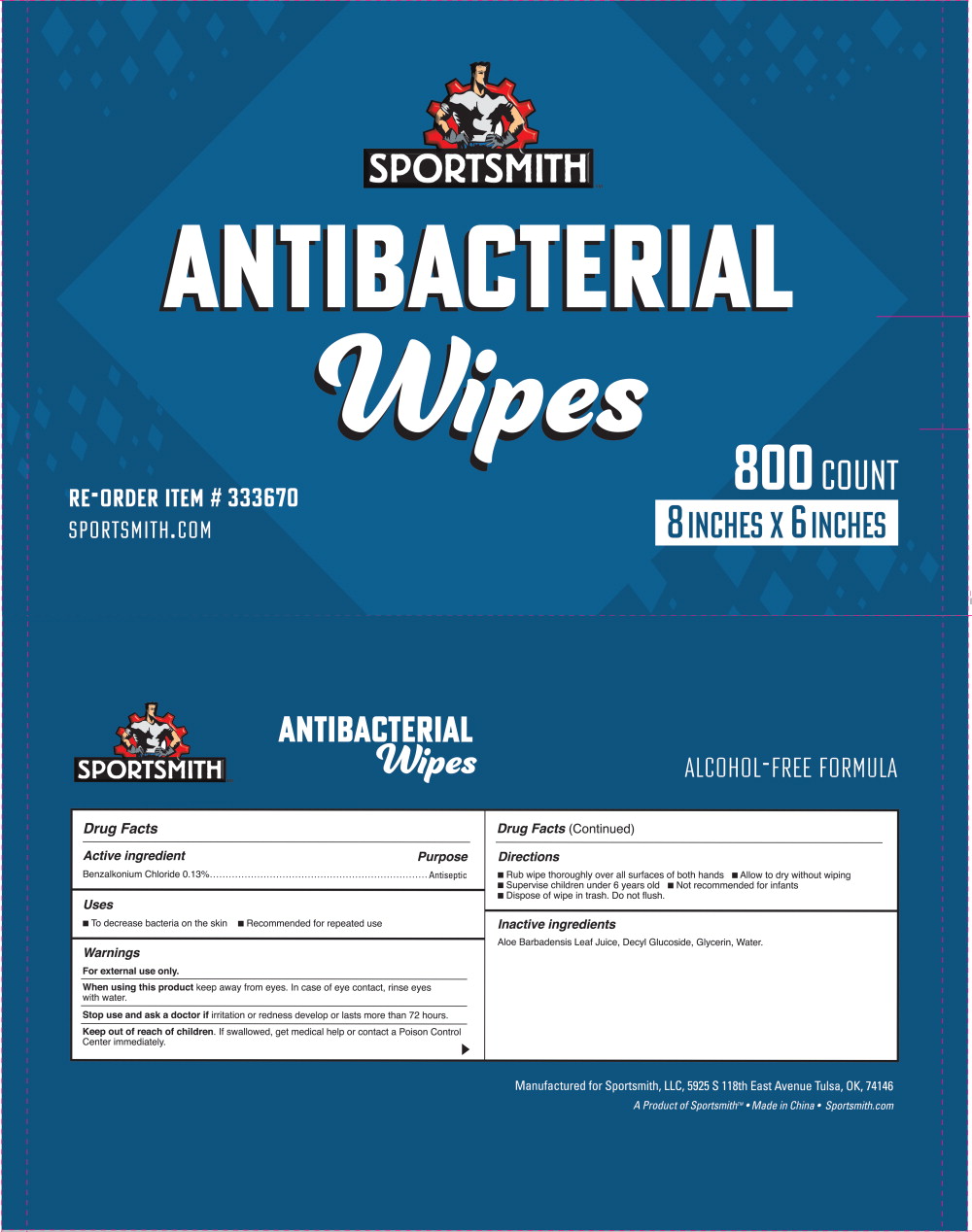 DRUG LABEL: Sanitising Wipes
NDC: 81331-001 | Form: CLOTH
Manufacturer: Sportsmith, L.L.C.
Category: otc | Type: HUMAN OTC DRUG LABEL
Date: 20250206

ACTIVE INGREDIENTS: BENZALKONIUM CHLORIDE 0.13 g/100 g
INACTIVE INGREDIENTS: ALOE VERA LEAF; DECYL GLUCOSIDE; GLYCERIN; WATER

Drug Facts

Active Ingredient

Benzalkonium Chloride 0.13%

Purpose

Antiseptic

Uses

- To decrease bacteria on the skin
- Recommended for repeated use

Warnings

For external use only.

When using this product keep away from eyes. In case of eye contact, rinse eyes with water.

Stop use and ask a doctor if irritation or redness develop or lasts more than 72 hours.

Keep out of reach of children. If swallowed, get medical help or contact a Poison Control Center immediately.

Directions

- Rub wipe thoroughly over all surfaces of both hands
- Allow to dry without wiping
- Supervise children under 6 years old
- Not recommended for infants
- Dispose of wipe in trash. Do not flush

Inactive Ingredients

Aloe Barbadensis Leaf Juice, Decyl Glucoside, Glycerin, Water

Principal Display Panel - 800 Count Bag Label

SPORTSMITH

ANTIBACTERIAL
Wipes

RE-ORDER ITEM # 333670

SPORTSMITH.COM

800 COUNT

8 INCHES X 6 INCHES